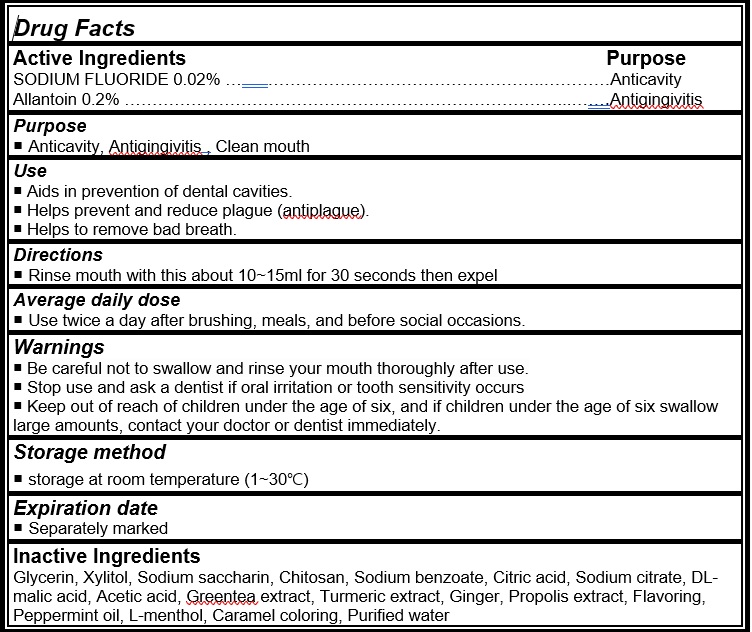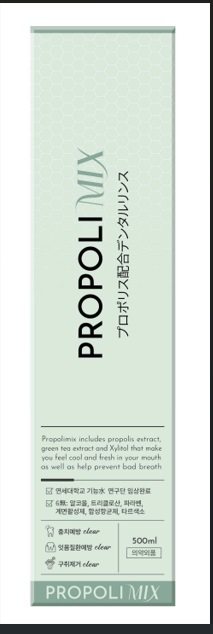 DRUG LABEL: Propolimix
NDC: 24765-002 | Form: LIQUID
Manufacturer: Pharmacal-International. Co., Ltd.
Category: otc | Type: HUMAN OTC DRUG LABEL
Date: 20241023

ACTIVE INGREDIENTS: SODIUM FLUORIDE 0.02 g/100 mL; ALLANTOIN 0.2 g/100 mL
INACTIVE INGREDIENTS: GLYCERIN; XYLITOL; SACCHARIN SODIUM; POLIGLUSAM; SODIUM BENZOATE; CITRIC ACID MONOHYDRATE; MALIC ACID; ACETIC ACID; GREEN TEA LEAF; TURMERIC; PROPOLIS WAX; PEPPERMINT OIL; 2-(L-MENTHOXY)ETHANOL; CARAMEL; WATER; GINGER

Active Ingredients Purpose

SODIUM FLUORIDE 0.02% ……..…………………………………………..…………Anticavity
Allantoin 0.2% ……………………………………………………………………...…..……Antigingivitis

Purpose

Anticavity, Antigingivitis, Clean mouth

Use

- Aids in prevention of dental cavities.
- Helps prevent and reduce plague (antiplague).
- Helps to remove bad breath.

Warnings

- Be careful not to swallow and rinse your mouth thoroughly after use.
- Stop use and ask a dentist if oral irritation or tooth sensitivity occurs
- Keep out of reach of children under the age of six, and if children under the age of six swallow large amounts, contact your doctor or dentist immediately.

Directions

Rinse mouth with this about 10~15ml for 30 seconds then expel

Average daily dose
Use twice a day after brushing, meals, and before social occasions.

Inactive Ingredients

Glycerin, Xylitol, Sodium saccharin, Chitosan, Sodium benzoate, Citric acid, Sodium citrate, DL-malic acid, Acetic acid, Greentea extract, Turmeric extract, Ginger tincture, Propolis extract, Flavoring, Peppermint oil, L-menthol, Caramel coloring, Purified water

Storage method

storage at room temperature (1~30℃)

Expiration date

Separately marked